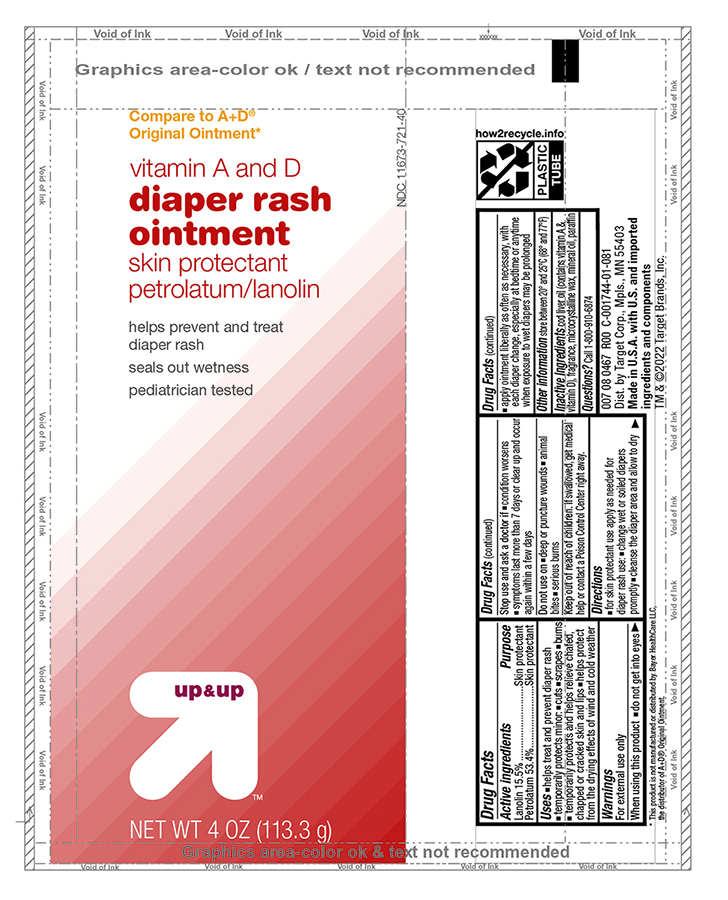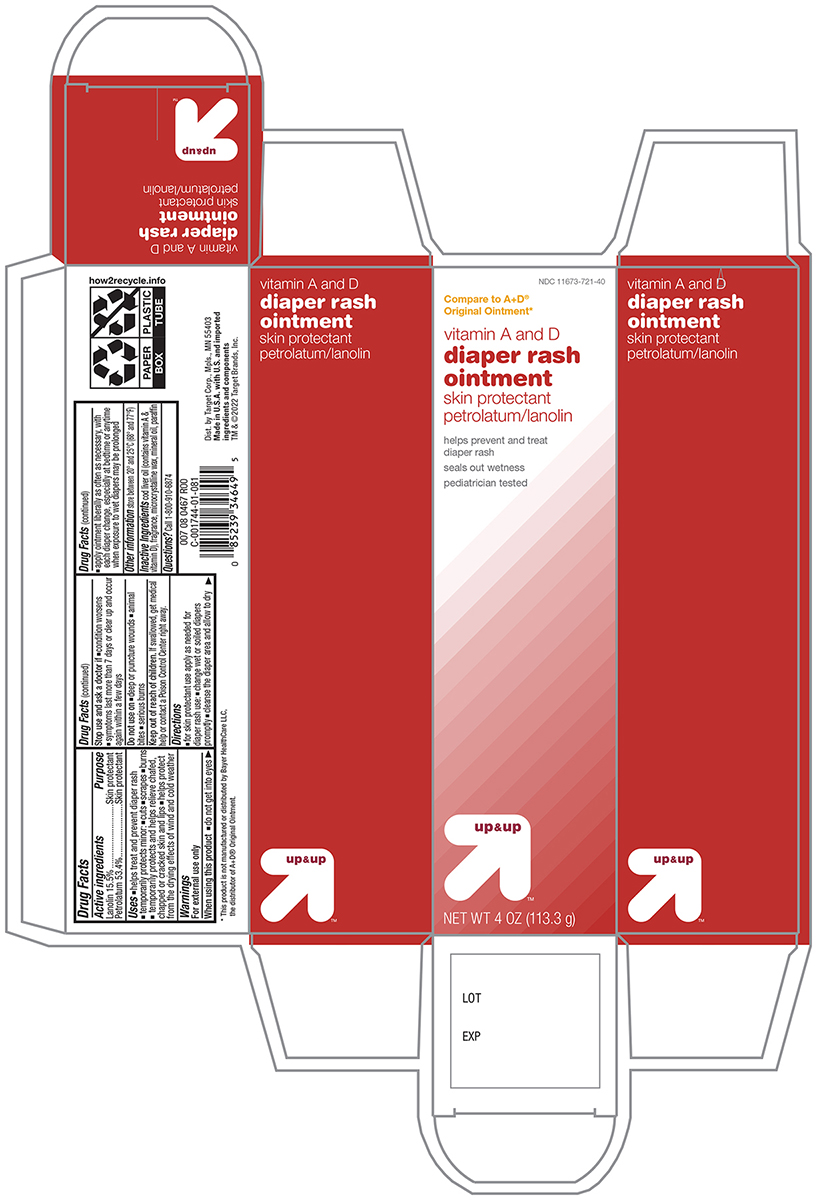 DRUG LABEL: Target Vitamin A and D Diaper Rash
NDC: 11673-721 | Form: OINTMENT
Manufacturer: Target Corporation
Category: otc | Type: HUMAN OTC DRUG LABEL
Date: 20241121

ACTIVE INGREDIENTS: PETROLATUM 534 mg/1 g; LANOLIN 155 mg/1 g
INACTIVE INGREDIENTS: COD LIVER OIL; MICROCRYSTALLINE WAX; MINERAL OIL; PARAFFIN

Active Ingredient

Petrolatum - 53.4 %

Lanolin - 15.5 %

Purpose

Skin Protectant

Uses

- helps treat and prevent diaper rash

temporarily protects minor:

- cuts
- scrapes
- burns

temporarily protects and helps relieve chafed, chapped or cracked skin and lips
helps protect from the drying effects of wind and cold weather

Warnings

For external use only

when using this product

- do not get into eyes

Stop use and ask a doctor if

- conditions worsens
- symptoms last more than 7 days or clear up and occur again within a few days

Do not use on

- deep or puncture wounds
- animal bites
- serious burns

Keep out of the reach of children

If swallowed, get medical help or contact a Poison Control Center right away.

Directions

- for skin protectant use apply as needed for diaper rash use
- change wet or soiled diapers promptly
- cleanse the diaper area and allow to dry
- apply ointment liberally as often as nessary, with each diaper change, especially at bedtime or anytime when exposed to wet diapers may be prolonged

Other information

store between 20° and 25°C (68° and 77°F)

Inactive ingredients

Cod Liver Oil (contains Vitamin A & Vitamin D), Fragrance, Microcrystalline Wax, Mineral Oil, Paraffin

Principal dispaly panel -Tube

Target Up and Up NDC 11673-721-40

Vitamin A&D ointment

Petrolatum 53.4%

Lanolin 15.5%

Skin protectant

NET WT 4.0 OZ (113.3g)

Principal display panel -Carton

Target Up and Up NDC 11673-721-40

Vitamin A&D ointment

Petrolatum 53.4%

Lanolin 15.5%

Skin protectant

NET WT 4.0 OZ (113.3g)